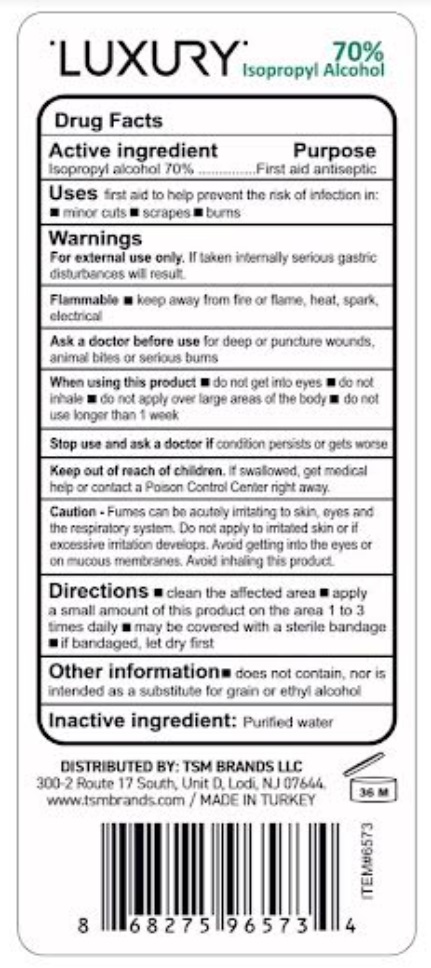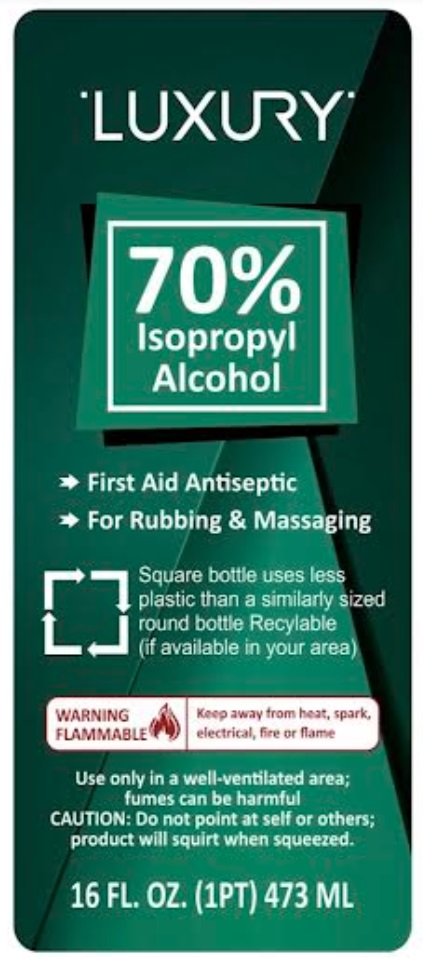 DRUG LABEL: LUXURY IPA 70%
NDC: 76567-2642 | Form: LIQUID
Manufacturer: TSM BRANDS LLC
Category: otc | Type: HUMAN OTC DRUG LABEL
Date: 20240916

ACTIVE INGREDIENTS: ISOPROPYL ALCOHOL 70 mL/100 mL
INACTIVE INGREDIENTS: WATER 30 mL/100 mL

Luxury Ipa 70%

Active Ingredient Purpose

Isopropyl Alcohol 70%.....First Aid anticeptic

Ask a doctor before use

for deep or puncture wounds, animal bites or serious burns.

Stop use and ask a doctor

If condition persists or gets worse

keep out of reach of children

if swallowed, get medical help or contact a poison control center right away

uses

First aid to help prevent the risk of infection in: minor cuts, scraps and burns

when using this product

Do not get into eyes, do not inhale, do not apply over large areas of the body. Do not use longer than one week.

warnings

For external use only. If taken internally, serious gastric disturbances will result.

Directions

Clean the affected area, apply a small amount of this product on the area 1,2 or 3 times daily. May be covered with a steryle bandage. If bandaged, let dry first.

Inactive Ingredient

Purified Water

Uses

First aid to help prevent the risk of infection in: minor cuts, scraps, burns